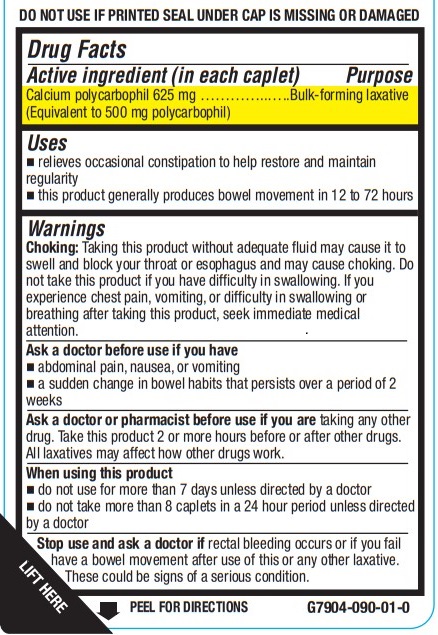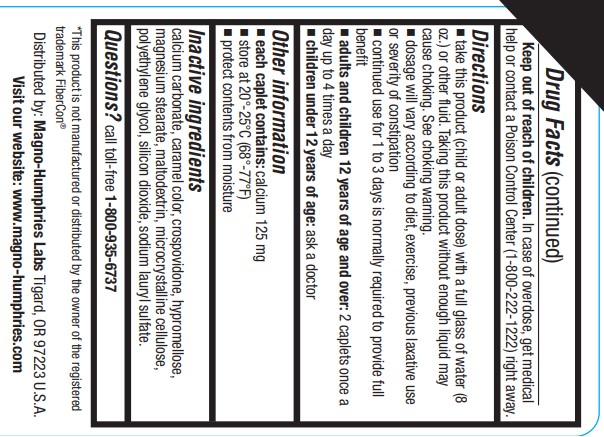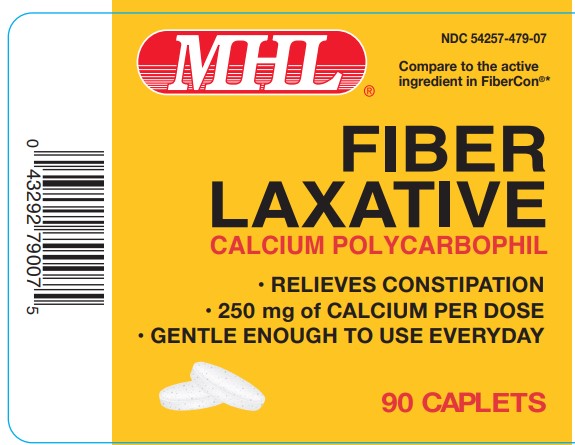 DRUG LABEL: FIBER LAXATIVE
NDC: 54257-479 | Form: TABLET
Manufacturer: Magno-Humphries, Inc.
Category: otc | Type: HUMAN OTC DRUG LABEL
Date: 20240103

ACTIVE INGREDIENTS: CALCIUM POLYCARBOPHIL 625 mg/1 1
INACTIVE INGREDIENTS: CALCIUM CARBONATE; CROSPOVIDONE; HYPROMELLOSE, UNSPECIFIED; CARAMEL; POLYETHYLENE GLYCOL, UNSPECIFIED; MAGNESIUM STEARATE; MALTODEXTRIN; MICROCRYSTALLINE CELLULOSE; SILICON DIOXIDE; SODIUM LAURYL SULFATE

MAGNO-HUMPHRIES - FIBER LAXATIVE (54257-479)

Active ingredient (in each caplet)

Calcium polycarbophil 625 mg

(Equivalent to 500 mg polycarbophil)

Purpose

Bulk-forming laxative

Uses

- relieves occasional constipation to help restore and maintain regularity
- this product generally produces bowel movement in 12 to 72 hours

Warnings

Choking: Taking this product without adequate fluid may cause it to swell and block your throat or esophagus and may cause choking. Do not take this product if you have difficulty in swallowing. If you experience chest pain, vomiting, or difficulty in swallowing or breathing after taking this product, seek immediate medical attention.

Ask a doctor before use if you have

- abdominal pain, nausea, or vomiting
- a sudden change in bowel habits that persists over a period of 2 weeks

Ask a doctor or pharmacist before use if you are taking any other drug. Take this product 2 or more hours before or after other drugs.
All laxatives may affect how other drugs work.

When using this product

- do not use for more than 7 days unless directed by a doctor
- do not take more than 8 caplets in a 24 hour period unless directed by a doctor

Stop use and ask a doctor if rectal bleeding occurs or if you fail to have a bowel movement after use of this or any other laxative. These could be signs of a serious condition.

Keep out of reach of children. In case of overdose, get medical help or contact a Poison Control Center (1-800-222-1222) right away.

Directions

- take this product (child or adult dose) with a full glass of water (8 oz.) or other fluid. Taking this product without enough liquid may

cause choking. See choking warning.

- dosage will vary according to diet, exercise, previous laxative use or severity of constipation
- continued use for 1 to 3 days is normally required to provide full benefit
- adults and children 12 years of age and over: 2 caplets once a day up to 4 times a day
- children under 12 years of age: ask a doctor

Other information

- each caplet contains: calcium 125 mg
- store at 20°-25°C (68°-77°F)
- protect contents from moisture

Inactive ingredients

calcium carbonate, caramel color, crospovidone, hypromellose, magnesium stearate, maltodextrin, microcrystalline cellulose,
polyethylene glycol, silicon dioxide, sodium lauryl sulfate.

Questions?

call toll-free 1-800-935-6737